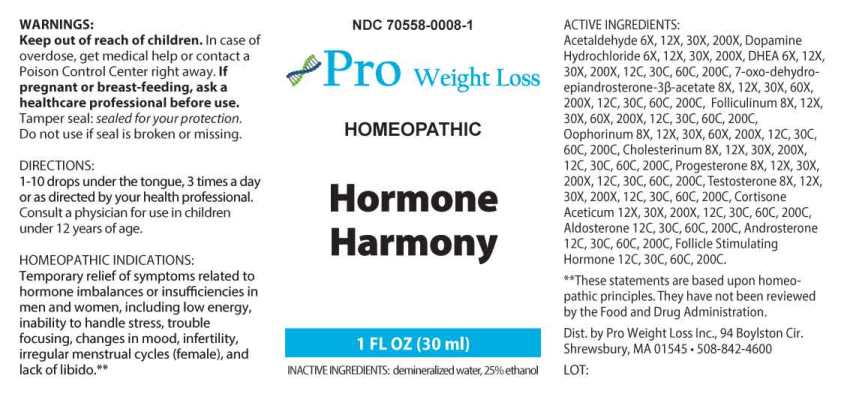 DRUG LABEL: Hormone Harmony
NDC: 70558-0008 | Form: LIQUID
Manufacturer: Pro Weight Loss Inc.
Category: homeopathic | Type: HUMAN OTC DRUG LABEL
Date: 20240122
DEA Schedule: CIII

ACTIVE INGREDIENTS: ACETALDEHYDE 6 [hp_X]/1 mL; DOPAMINE HYDROCHLORIDE 6 [hp_X]/1 mL; PRASTERONE 6 [hp_X]/1 mL; 7-KETO-DEHYDROEPIANDROSTERONE 8 [hp_X]/1 mL; ESTRONE 8 [hp_X]/1 mL; SUS SCROFA OVARY 8 [hp_X]/1 mL; CHOLESTEROL 8 [hp_X]/1 mL; PROGESTERONE 8 [hp_X]/1 mL; TESTOSTERONE 8 [hp_X]/1 mL; CORTISONE ACETATE 12 [hp_X]/1 mL; ALDOSTERONE 12 [hp_C]/1 mL; ANDROSTERONE 12 [hp_C]/1 mL; FOLLITROPIN 12 [hp_C]/1 mL
INACTIVE INGREDIENTS: WATER; ALCOHOL

DRUG FACTS:

ACTIVE INGREDIENTS:

Acetaldehyde 6X, 12X, 30X, 200X, Dopamine Hydrochloride 6X, 12X, 30X, 200X, DHEA (Dehydroepiandrosterone) 6X, 12X, 30X, 200X, 12C, 30C, 60C, 200C, 7-Oxo-Dehydroepiandrosterone 3β-Acetate, 8X, 12X, 30X, 60X, 200X, 12C, 30C, 60C, 200C, Folliculinum 8X, 12X, 30X, 60X, 200X, 12C, 30C, 60C, 200C, Oophorinum (Suis) 8X, 12X, 30X, 60X, 200X, 12C, 30C, 60C, 200C, Cholesterinum 8X, 12X, 30X, 200X, 12C, 30C, 60C, 200C, Progesterone 8X, 12X, 30X, 200X, 12C, 30C, 60C, 200C, Testosterone 8X, 12X, 30X, 200X, 12C, 30C, 60C, 200C, Cortisone Aceticum 12X, 30X, 200X, 12C, 30C, 60C, 200C, Aldosterone 12C, 30C, 60C, 200C, Androsterone 12C, 30C, 60C, 200C, Follicle Stimulating Hormone 12C, 30C, 60C, 200C.

HOMEOPATHIC INDICATIONS:

Temporary relief of symptoms related to hormone imbalances of insufficiencies in men and women, including low energy, inability to handle stress, trouble focusing, changes in mood, infertility, irregular menstrual cycles (females), and lack of libido.**

**These statements are based upon homeopathic principles. They have not been reviewed by the Food and Drug Administration.

WARNINGS:

Keep out of reach of children. In case of overdose, get medical help or contact a Poison Control Center right away.

If pregnant or breast-feeding, ask a healthcare professional before use.

Tamper seal: sealed for your protection.

Do not use if seal is broken or missing.

Keep out of reach of children. In case of overdose, get medical help or contact a Poison Control Center right away.

DIRECTIONS:

1-10 drops under the tongue, 3 times a day or as directed by your health professional. Consult a physician for use in children under 12 years of age.

HOMEOPATHIC INDICATIONS:

Temporary relief of symptoms related to hormone imbalances of insufficiencies in men and women, including low energy, inability to handle stress, trouble focusing, changes in mood, infertility, irregular menstrual cycles (females), and lack of libido.**

**These statements are based upon homeopathic principles. They have not been reviewed by the Food and Drug Administration.

INACTIVE INGREDIENTS:

demineralized water, 25% ethanol

QUESTIONS:

Dist. by

Pro Weight Loss Inc., 94 Boylston Cir.

Shrewsbury, MA 01545 • 508-842-4600

PACKAGE LABEL DISPLAY:

NDC 70558-0008-1

Pro Weight Loss

HOMEOPATHIC

Hormone Harmony

1 FL OZ (30 ml)